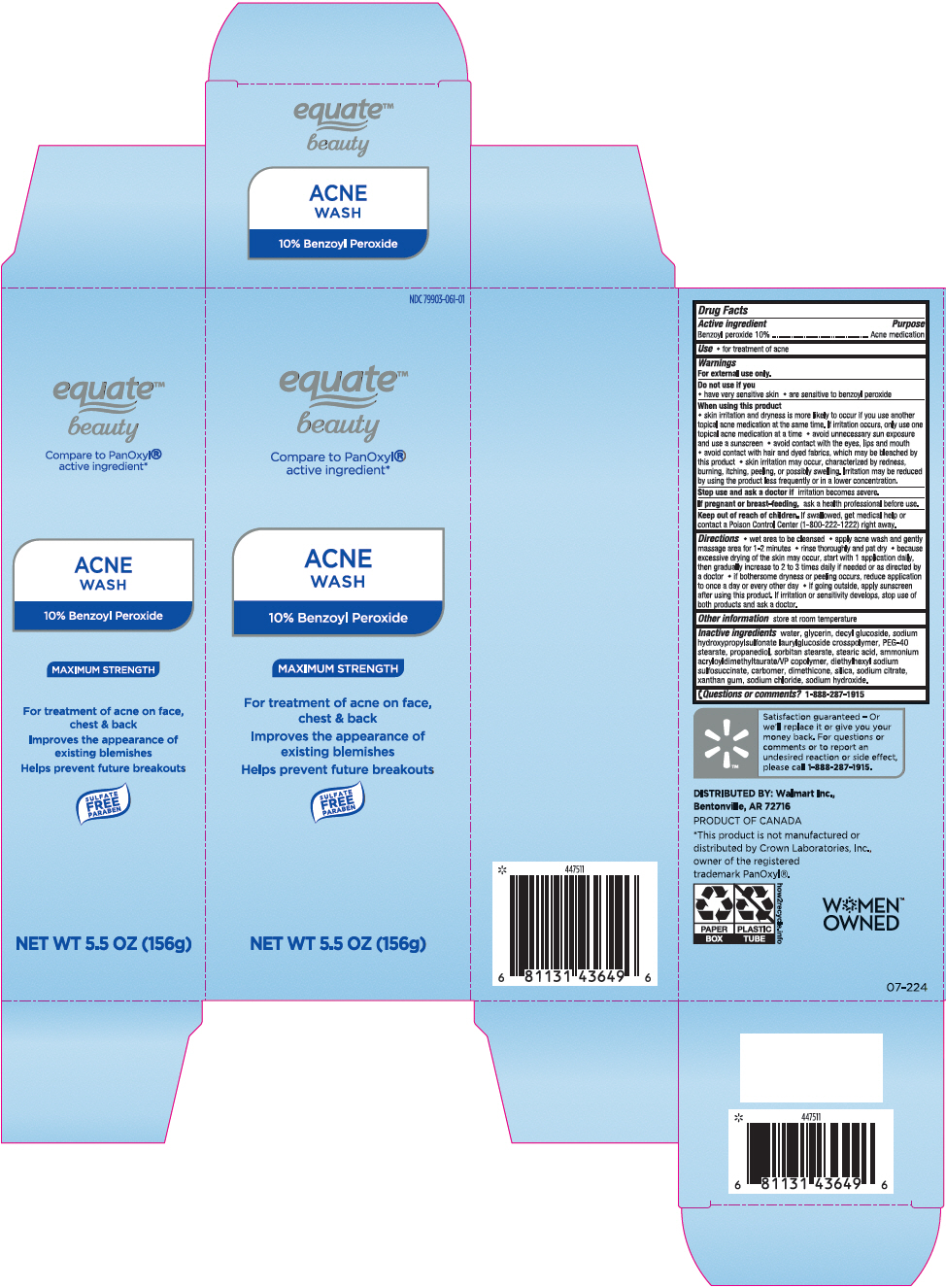 DRUG LABEL: Equate Acne Wash
NDC: 79903-061 | Form: CREAM
Manufacturer: Wal-Mart Stores, Inc.
Category: otc | Type: HUMAN OTC DRUG LABEL
Date: 20241118

ACTIVE INGREDIENTS: Benzoyl Peroxide 100 mg/1 g
INACTIVE INGREDIENTS: Water; Glycerin; Decyl Glucoside; SODIUM DECYLGLUCOSIDES HYDROXYPROPYLSULFONATE; PEG-40 MONOSTEARATE; Propanediol; SORBITAN MONOSTEARATE; Stearic Acid; Ammonium Acryloyldimethyltaurate/VP Copolymer; DOCUSATE SODIUM; CARBOMER HOMOPOLYMER, UNSPECIFIED TYPE; Dimethicone; SILICON DIOXIDE; SODIUM CITRATE, UNSPECIFIED FORM; Xanthan Gum; Sodium Chloride; Sodium Hydroxide

Equate™ Acne Wash
Acne medication

Drug Facts

Active ingredient

Benzoyl Peroxide 10%

Purpose

Acne medication

Use

- for treatment of acne

Warnings

For external use only

Do not use if you

- have very sensitive skin
- are sensitive to benzoyl peroxide

When using this product

- skin irritation and dryness is more likely to occur if you use another topical acne medication at the same time. If irritation occurs, only use one topical acne medication at a time
- avoid unnecessary sun exposure and use a sunscreen
- avoid contact with the eyes, lips and mouth
- avoid contact with hair or dyed fabrics, which may be bleached by this product
- skin irritation may occur, characterized by redness, burning, itching, peeling, or possibly swelling. Irritation may be reduced by using the product less frequently or in a lower concentration.

Stop use and ask a doctor if irritation becomes severe.

PREGNANCY OR BREAST FEEDING

If pregnant or breast-feeding, ask a health professional before use.

Keep out of reach of children. If swallowed, get medical help or contact a Poison Control Center (1-800-222-1222) right away.

Directions

- wet area to be cleansed
- apply acne wash and gently massage area for 1-2 minutes
- rinse thoroughly and pat dry
- because excessive drying of the skin may occur, start with 1 application daily, then gradually increase to 2 to 3 times daily if needed or as directed by a doctor
- if bothersome dryness or peeling occurs, reduce application to once a day or every other day
- if going outside, apply sunscreen after using this product. If irritation or sensitivity develops, stop use of both products and ask a doctor.

Other information

Store at room temperature

Inactive ingredients

water, Glycerin, decyl glucoside, sodium hydroxypropylsulfonate laurylglucoside crosspolymer, PEG-40 stearate, propanediol, sorbitan stearate, stearic acid, ammonium acryloyldimethyltaurate/VP copolymer, diethylhexyl sodium sulfosuccinate, carbomer, dimethicone, silica, sodium citrate, xanthan gum, sodium chloride, sodium hydroxide.

Questions or comments?

1-888-287-1915

DISTRIBUTED BY: Walmart Inc.,
Bentonville, AR 72716

PRINCIPAL DISPLAY PANEL - 156 g Tube Carton

NDC 79903-061-01

equate™
beauty

Compare to PanOxyl®
active ingredient*

ACNE
WASH
10% Benzoyl Peroxide

MAXIMUM STRENGTH

For treatment of acne on face,
chest & back
Improves the appearance of
existing blemishes
Helps prevent future breakouts

SULFATE
FREE
PARABEN

NET WT 5.5 OZ (156g)